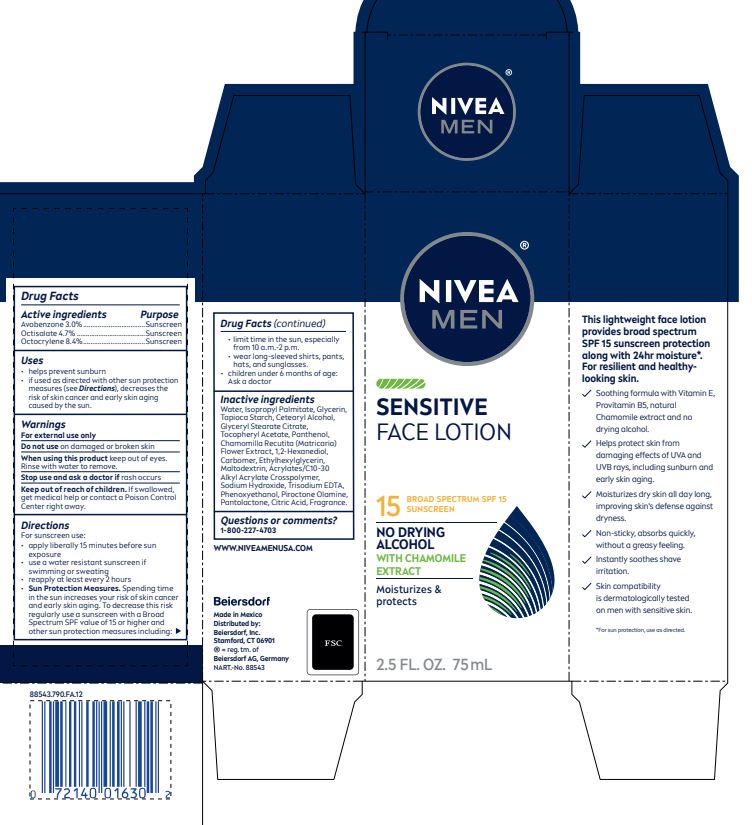 DRUG LABEL: Nivea Men Sensitive Protective
NDC: 10356-575 | Form: LOTION
Manufacturer: Beiersdorf Inc
Category: otc | Type: HUMAN OTC DRUG LABEL
Date: 20251231

ACTIVE INGREDIENTS: AVOBENZONE 3 g/100 mL; OCTISALATE 4.7 g/100 mL; OCTOCRYLENE 8.4 g/100 mL
INACTIVE INGREDIENTS: HEXANEDIOL; CARBOMER HOMOPOLYMER TYPE C (ALLYL PENTAERYTHRITOL CROSSLINKED); ETHYLHEXYLGLYCERIN; MALTODEXTRIN; CARBOMER INTERPOLYMER TYPE A (ALLYL SUCROSE CROSSLINKED); SODIUM HYDROXIDE; EDETATE TRISODIUM; PHENOXYETHANOL; PIROCTONE OLAMINE; WATER; ISOPROPYL PALMITATE; GLYCERIN; STARCH, TAPIOCA; CETOSTEARYL ALCOHOL; GLYCERYL STEARATE CITRATE; .ALPHA.-TOCOPHEROL ACETATE, DL-; PANTHENOL; CHAMOMILE

Nivea Men Sensitive Face

Active ingredients
Avobenzone 3%
Octisalate 4.7%
Octocrylene 8.4%

Purpose
Sunscreen

Uses
• helps prevent sunburn
• if used as directed with other sun protection measures (see Directions),
decreases the risk of skin cancer and early skin aging caused by the sun.

Warnings
For external use only

Do not use on damaged or broken skin

When using this product keep out of eyes.
Rinse with water to remove.

Stop use and ask a doctor if rash occurs

Keep out of reach of children. If swallowed,
get medical help or contact a Poison Control
Center right away.

Questions or comments?
1-800-227-4703

Directions
For sunscreen use:
• apply liberally 15 minutes before sun exposure
• use a water resistant sunscreen if swimming or sweating
• reapply at least every 2 hours
• Sun Protection Measures. Spending time in the sun increases your risk of skin
cancer and early skin aging. To decrease this risk regularly use a sunscreen with
a Broad Spectrum SPF value of 15 or higher and other sun protection
measures including: • limit time in the sun, especially from
10 a.m.-2 p.m. • wear long-sleeved shirts, pants, hats, and sunglasses.
• children under 6 months of age: Ask a doctor

Inactive ingredients
Water, Isopropyl Palmitate,Glycerin, Tapioca Starch, Cetearyl
Alcohol, Glyceryl Stearate Citrate, Tocopheryl Acetate, Panthenol,
Chamomilla Recutita (Matricaria) Flower Extract, 1,2-Hexanediol, Carbomer,
Ethylhexylglycerin, Maltodextrin, Acrylates/Cl0-30 Alkyl Acrylate Crosspolymer, Sodium Hydroxide,
Trisodium EDTA, Phenoxyethanol, Piroctone OIamine, Fragrance.

PACKAGE LABEL

NIVEA MEN

Sensitive

Face Lotion

Broad Spectrum SPF 15

Sunscreen

No Drying Alcohol

with Chamomile Extract

Moisturizes and Protects